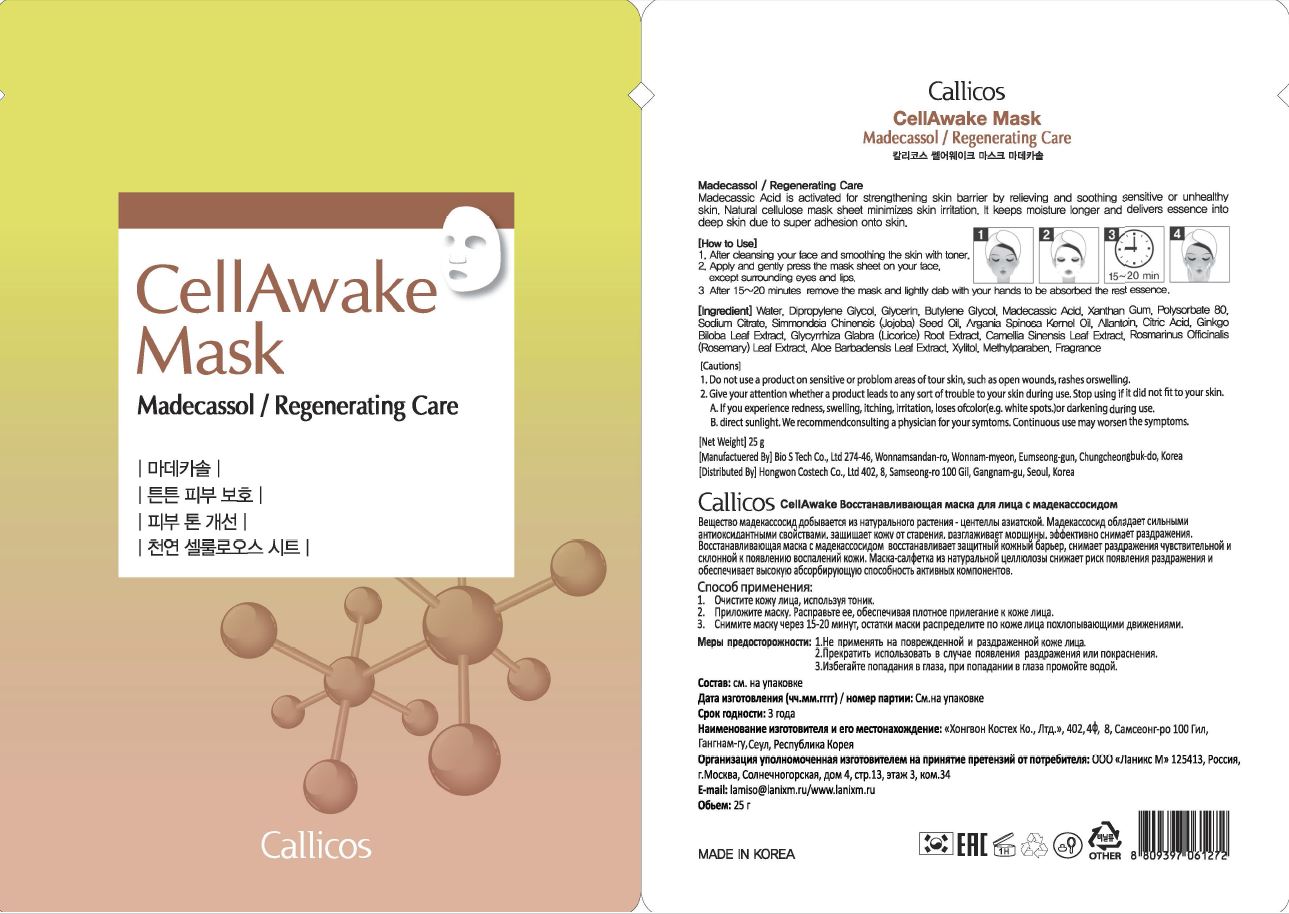 DRUG LABEL: Callicos CellAwake Mask madecassol
NDC: 74647-0006 | Form: LIQUID
Manufacturer: HONGWON COSTECH CO.,LTD
Category: otc | Type: HUMAN OTC DRUG LABEL
Date: 20210402

ACTIVE INGREDIENTS: MADECASSIC ACID 0.04 g/100 g
INACTIVE INGREDIENTS: GLYCERIN; BUTYLENE GLYCOL

ACTIVE INGREDIENTS

Madecassic Acid

INACTIVE INGREDIENTS

Water. Dipropylene Glycol. Glycerin. Butylene glycol. xanthan gum, polysorbate 80. Sodium Citrate, Simmondsia Chinensis (Jojoba) Seed Oil, Argania Spinosa Kernel Oil, Allantoin, Crtric alcid, Ginkgo Biloba Leaf Extract. Glycyrrhiza Glabra (Licorice) Root Extract. camellia Sinensis Leaf Extract, Rosmarinus Ofiicinalis (Rosemary) Leaf Extract, Aloe Barbadensis Leaf Extract, Xylitol. Methylparaben. Fragrance

PURPOSE

wrinkle care

WARNINGS

1. Consult a physician if red spots, swollenness, itchiness, or any other abnormal symptoms or side effects develops on the applied area during or after use or under direct sunlight.

2. Do not use on wound, etc.

3. Precautions for handling and storage

a) Keep out of the reach of children

b) Avoid direct sunlight

KEEP OUT OF REACH OF CHILDREN

Uses

after cleansing your face and smoothing the skin with toner

apply and gently press the mask sheet on your face except surrounding eyes and lips

after 15-20 minutes, remove the mask and lightly dab with your hands to be absorbed the rest essence

Directions

for external use only